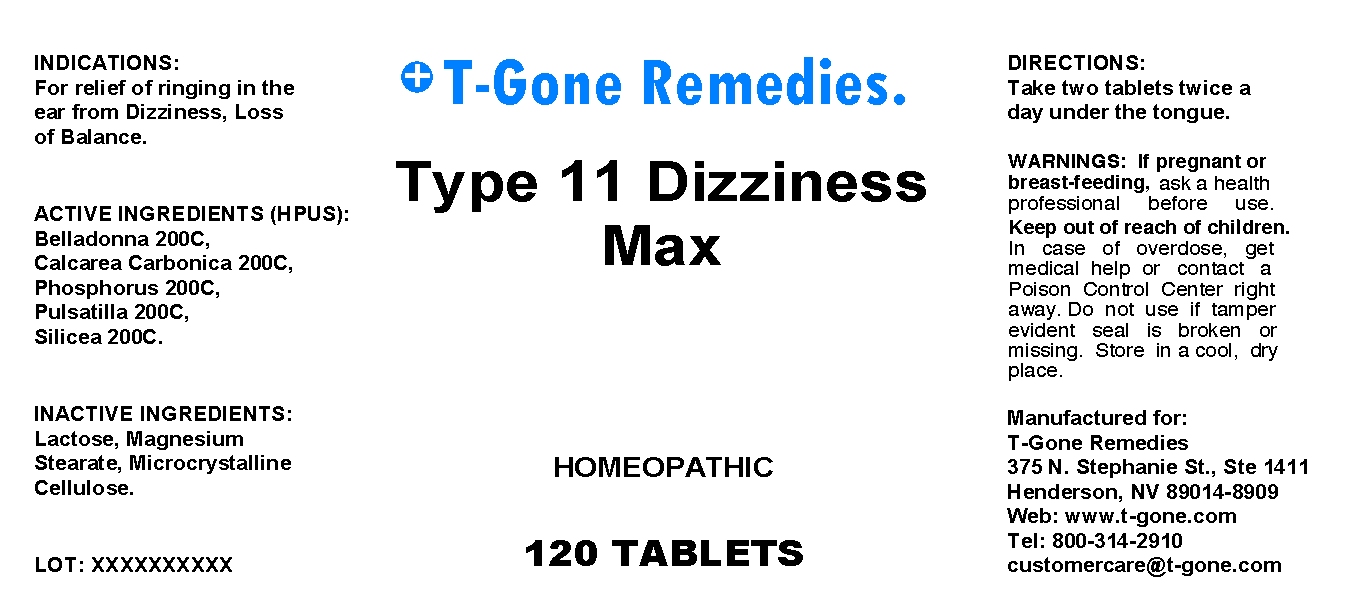 DRUG LABEL: Type 11 Dizziness Max
NDC: 57520-0432 | Form: TABLET
Manufacturer: Apotheca Company
Category: homeopathic | Type: HUMAN OTC DRUG LABEL
Date: 20100715

ACTIVE INGREDIENTS: ATROPA BELLADONNA 200 [hp_C]/1 mg; OYSTER SHELL CALCIUM CARBONATE, CRUDE 200 [hp_C]/1 mg; PHOSPHORUS 200 [hp_C]/1 mg; PULSATILLA VULGARIS 200 [hp_C]/1 mg; SILICON DIOXIDE 200 [hp_C]/1 mg
INACTIVE INGREDIENTS: LACTOSE; MAGNESIUM STEARATE; CELLULOSE, MICROCRYSTALLINE

Type 11 Dizziness Max

ACTIVE INGREDIENT

ACTIVE INGREDIENTS: Belladonna 200C, Calcarea carbonica 200C, Phosphorus 200C, Pulsatilla 200C, Silicea 200C.

PURPOSE

INDICATIONS: For relief of ringing in the ear from Dizziness, Loss of Balance.

WARNINGS

WARNINGS: If pregnant or breast-feeding, ask a health professional before use.

DOSAGE AND ADMINISTRATION

DIRECTIONS: Take two tablets twice a day under the tongue.

INACTIVE INGREDIENT

INACTIVE INGREDIENTS: Lactose, Magnesium stearate, Microcrystalline cellulose.

QUESTIONS

Manufactured for:

T-Gone Remedies

375 N. Stephanie St., Ste 1411

Henderson, NV 89014-8909

Web: www.t-gone.com

Tel: 800-314-2910

customercare@t-gone.com

PACKAGE LABEL

T-Gone Remedies.

Type 11 Dizziness Max

HOMEOPATHIC

120 TABLETS